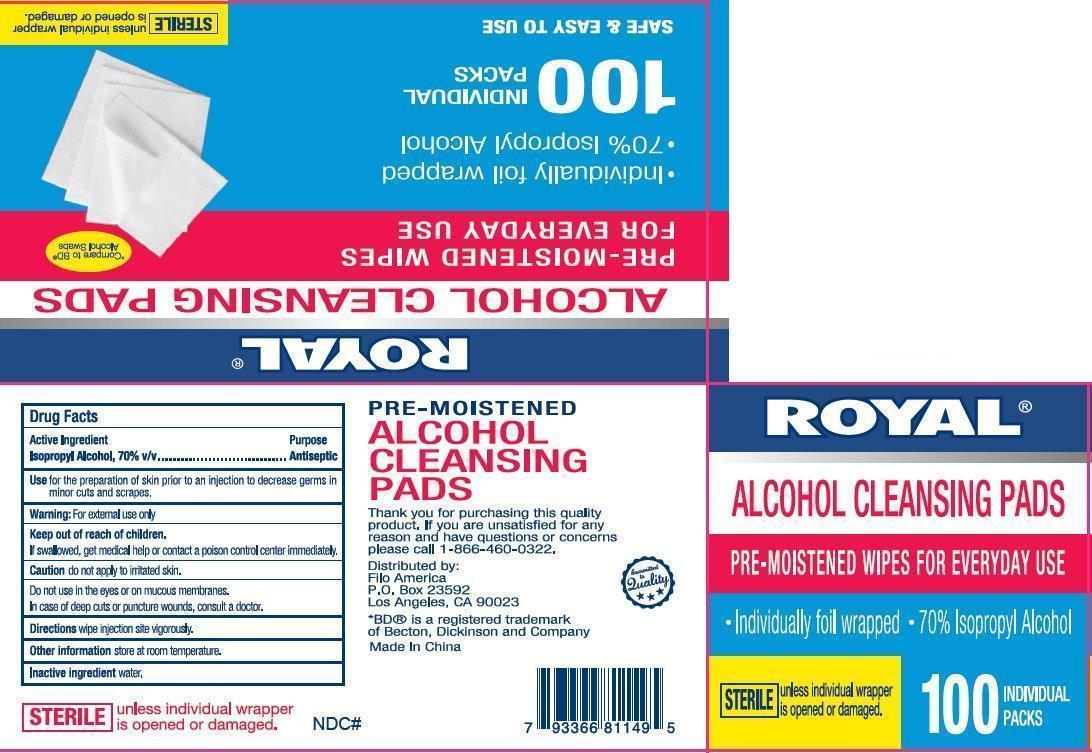 DRUG LABEL: ROYAL ALCOHOL CLEANSING PADS
NDC: 50438-000 | Form: LIQUID
Manufacturer: Filo America
Category: otc | Type: HUMAN OTC DRUG LABEL
Date: 20130731

ACTIVE INGREDIENTS: ISOPROPYL ALCOHOL 0.45 mg/1 g
INACTIVE INGREDIENTS: WATER

ROYAL ALCOHOL CLEANSING PADS

Active Ingredient

Isopropyl Alcohol, 70% v/v

Purpose

Antiseptic

Use

for the preparation of skin prior to an injection to decrease germs in minor cuts and scrapes.

Warning:

For external use only

Keep out of reach of children.

If swallowed, get medical help or contact a poison control center immediately.

Caution

do not apply to irritated skin.

Do not use

in the eyes or on mucous membranes.

In case

of deep cuts or puncture wounds, consult a doctor.

Direction

wipe injection site vigorously.

Other information

store at room temperature.

Inactive ingredient

water

PACKAGE LABEL

ROYAL ALCOHOL CLEANSING PADS
PRE-MOISTENED WIPES FOR EVERYDAY USE

- Individually foil wrapped
- 70% Isopropyl Alcohol

100 INDIVIDUAL PACKS
SAFE AND EAST TO USE
STERILE unless individual wrapper is opened or damaged.